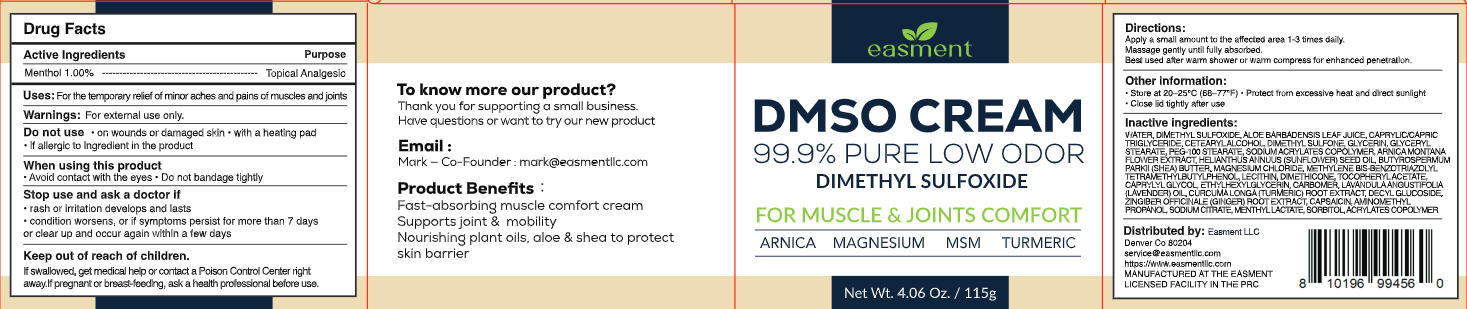 DRUG LABEL: Easment DMSO cream
NDC: 87352-002 | Form: CREAM
Manufacturer: Easment LLC
Category: otc | Type: HUMAN OTC DRUG LABEL
Date: 20260122

ACTIVE INGREDIENTS: MENTHOL 1.15 g/115 g
INACTIVE INGREDIENTS: PEG-100 STEARATE; GINGER; CAPRYLIC/CAPRIC TRIGLYCERIDE; METHYLENE BIS-BENZOTRIAZOLYL TETRAMETHYLBUTYLPHENOL; MAGNESIUM CHLORIDE; CAPSAICIN; AMINOMETHYLPROPANOL; ETHYLHEXYLGLYCERIN; SODIUM ACRYLATES CROSSPOLYMER-2; DIMETHYL SULFONE; CURCUMA LONGA (TURMERIC) ROOT; WATER; CETEARYL ALCOHOL; GLYCERIN; GLYCERYL STEARATE; CARBOMER; LAVANDULA ANGUSTIFOLIA (LAVENDER) OIL; BUTYROSPERMUM PARKII (SHEA) BUTTER; LECITHIN, SOYBEAN; DIMETHICONE 1000; CAPRYLYL GLYCOL; GLATIRAMER ACETATE; ALOE BARBADENSIS LEAF JUICE; ARNICA MONTANA FLOWER WATER; HELIANTHUS ANNUUS (SUNFLOWER) SEED OIL; ALPHA-TOCOPHEROL ACETATE; DECYL GLUCOSIDE

Easment DMSO CREAM-Initial-158

ACTIVE INGREDIENT

Menthol 1.00%

PURPOSE

Topical Analgesic

DOSAGE AND ADMINISTRATION

For the temporary relief of minor aches and pains of muscles and joints.

WARNINGS

For external use only.

DO NOT USE

- on wounds or damaged skin
- with a heating pad
- if allergic to ingredient in the product

WHEN USING

- Avoidcontact with the eyes
- Do not bandage tightly

ASK DOCTOR

- rash or irritation developsand lasts
- condition worsens, or if symptoms persist for more than 7 days or clear up ad occur again within a few days

KEEP OUT OF REACH OF CHILDREN

If swallowed, get medical help or contact a Poison Control Center right away. If pregnant or breast-feeding, ask a health professional before use.

INDICATIONS AND USAGE

- Apply a small amount to the affected area 1-3 times daily.
- Massage gently until fully absorbed.
- Best used after warm shower or warm compress for enhanced penetration.

OTHER SAFETY INFORMATION

- Store at 20-25°C(68-77°F)
- Protect from excessive heat and direct sunlight
- Close lidtightly after use

INACTIVE INGREDIENT

WATER, DIMETHYL SULFOXIDE, ALOE BARBADENSIS LEAF JUICE, CAPRYLIC/CAPRICTRI GLYCERIDE, CETEARYL ALCOHOL DIMETHYL SULFONE, GLYCERIN, GLYCERYLSTEARATE, PEG-100 STEARATE, SODIUM ACRYLATES COPOLYMER, ARNICA MONTANA FLOWER EXTRACT, HELIANTHUS ANNUUS (SUNFLOWER) SEED OIL, BUTYROSPERMUMPARKII (SHEA) BUTTER, MAGNESIUM CHLORIDE, METHYLENE BIS-BENZOTRIAZOLYLTETRAMETHYLBUTYLPHENOL LECITHIN, DIMETHICONE, TOCOPHERYL ACETATE,CAPRYLYL GLYCOL, ETHYLHEXYLGLYCERIN, CARBOMER, LAVANDULAANGUSTIFOLIA(LAVENDER) OIL CURCUMALONGA(TURMERIC) ROOT EXTRACT, DECYL GLUCOSIDE,ZINGIBER OFFICINALE (GINGER) ROOT EXTRACT, CAPSAICIN, AMINOMETHYLPROPANOL, SODIUM CITRATE, MENTHYL LACTATE, SORBITOL, ACRYLATES COPOLYMER